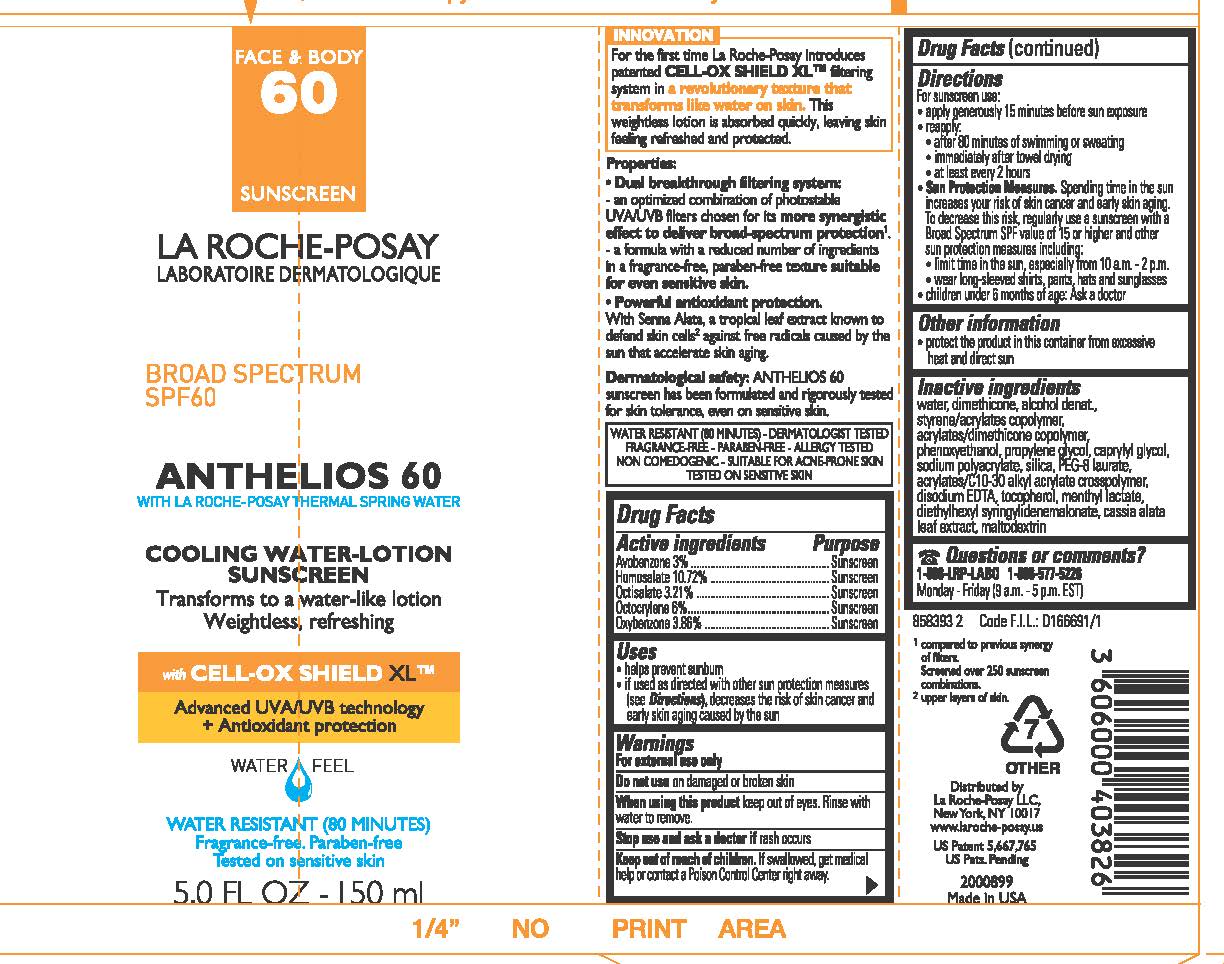 DRUG LABEL: La Roche Posay Laboratoire Dermatologique Anthelios 60 Face and Body Cooling Water Broad Spectrum SPF 60 Sunscreen Water Resistant 80 Minutes
NDC: 49967-038 | Form: LOTION
Manufacturer: L'Oreal USA Products Inc
Category: otc | Type: HUMAN OTC DRUG LABEL
Date: 20231231

ACTIVE INGREDIENTS: AVOBENZONE 30 mg/1 mL; HOMOSALATE 107.2 mg/1 mL; OCTISALATE 32.1 mg/1 mL; OCTOCRYLENE 60 mg/1 mL; OXYBENZONE 38.6 mg/1 mL
INACTIVE INGREDIENTS: WATER; DIMETHICONE; ALCOHOL; PHENOXYETHANOL; PROPYLENE GLYCOL; CAPRYLYL GLYCOL; PEG-8 LAURATE; TOCOPHEROL; DIETHYLHEXYL SYRINGYLIDENEMALONATE; MALTODEXTRIN

Drug Facts

Active ingredient

Avobenzone 3%

Homosalate 10.72%

Octisalate 3.21%

Octocrylene 6%

Oxybenzone 3.86

Purpose

Sunscreen

Uses

- helps prevent sunburn
- if used as directed with other sun protection measures (see Directions), decreases the risk of skin cancer and early skin aging caused by the sun

Warnings

For external use only

Do not use

on damaged or broken skin

When using this product

keep out of eyes. Rinse with water to remove.

Stop use and ask a doctor if

rash occurs

Keep out of reach of children.

If swallowed, get medical help or contact a Poison Control Center right away.

Directions

For sunscreen use:

● apply generously 15 minutes before sun exposure

● reapply:

● after 80 minutes of swimming or sweating

● immediately after towel drying

● at least every 2 hours

● Sun Protection Measures. Spending time in the sun increases your risk of skin cancer and early skin aging. To decrease this risk, regularly use a sunscreen with a Broad Spectrum SPF value of 15 or higher and other sun protection measures including:

● limit time in the sun, especially from 10 a.m. – 2 p.m.

● wear long-sleeved shirts, pants, hats, and sunglasses

● children under 6 months of age: Ask a doctor

Other information

protect the product in this container from excessive heat and direct sun

Inactive ingredients

water, dimethicone, alcohol denat., styrene/acrylates copolymer, acrylates/dimethicone copolymer, phenoxyethanol, propylene glycol, caprylyl glycol, sodium polyacrylate, silica, PEG-8 laurate, acrylates/C10-30 alkyl acrylate crosspolymer, disodium EDTA, tocopherol, menthyl lactate, diethylhexyl syringylidenemalonate, cassia alata leaf extract, maltodextrin

Questions or comments?

1-888-LRP-LABO 1-888-577-5226

Monday - Friday (9 a.m. - 5 p.m. EST)